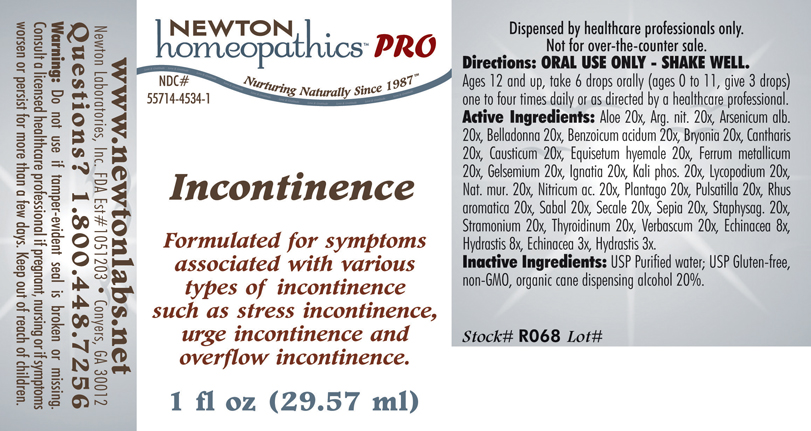 DRUG LABEL: Incontinence 
NDC: 55714-4534 | Form: LIQUID
Manufacturer: Newton Laboratories, Inc.
Category: homeopathic | Type: HUMAN PRESCRIPTION DRUG LABEL
Date: 20110601

ACTIVE INGREDIENTS: Aloe 20 [hp_X]/1 mL; Silver Nitrate 20 [hp_X]/1 mL; Arsenic Trioxide 20 [hp_X]/1 mL; Atropa Belladonna 20 [hp_X]/1 mL; Benzoic Acid 20 [hp_X]/1 mL; Bryonia Alba Root 20 [hp_X]/1 mL; Lytta Vesicatoria 20 [hp_X]/1 mL; Causticum 20 [hp_X]/1 mL; Equisetum Hyemale 20 [hp_X]/1 mL; Iron 20 [hp_X]/1 mL; Gelsemium Sempervirens Root 20 [hp_X]/1 mL; Strychnos Ignatii Seed 20 [hp_X]/1 mL; Potassium Phosphate, Dibasic 20 [hp_X]/1 mL; Lycopodium Clavatum Spore 20 [hp_X]/1 mL; Sodium Chloride 20 [hp_X]/1 mL; Nitric Acid 20 [hp_X]/1 mL; Plantago Major 20 [hp_X]/1 mL; Pulsatilla Vulgaris 20 [hp_X]/1 mL; Rhus Aromatica Root Bark 20 [hp_X]/1 mL; Saw Palmetto 20 [hp_X]/1 mL; Claviceps Purpurea Sclerotium 20 [hp_X]/1 mL; Sepia Officinalis Juice 20 [hp_X]/1 mL; Delphinium Staphisagria Seed 20 [hp_X]/1 mL; Datura Stramonium 20 [hp_X]/1 mL; Thyroid, Unspecified 20 [hp_X]/1 mL; Verbascum Thapsus 20 [hp_X]/1 mL; Echinacea, Unspecified 8 [hp_X]/1 mL; Goldenseal 8 [hp_X]/1 mL
INACTIVE INGREDIENTS: Alcohol

Incontinence

INDICATIONS & USAGE SECTION

Incontinence Formulated for symptoms associated with various types of incontinence such as stress incontinence, urge incontinence and overflow incontinence.

DOSAGE & ADMINISTRATION SECTION

Directions: ORAL USE ONLY - SHAKE WELL. Ages 12 and up, take 6 drops orally (ages 0 to 11, give 3 drops) one to four times daily or as directed by a healthcare professional.

ACTIVE INGREDIENT SECTION

Aloe 20x, Arg. nit. 20x, Arsenicum alb. 20x, Belladonna 20x, Benzoicum acidum 20x, Bryonia 20x, Cantharis 20x, Causticum 20x, Equisetum hyemale 20x, Ferrum metallicum 20x, Gelsemium 20x, Ignatia 20x, Kali phos. 20x, Lycopodium 20x, Nat. mur. 20x, Nitricum ac. 20x, Plantago 20x, Pulsatilla 20x, Rhus aromatica 20x, Sabal 20x, Secale 20x, Sepia 20x, Staphysag. 20x, Stramonium 20x, Thyroidinum 20x, Verbascum 20x, Echinacea 8x, Hydrastis 8x, Echinacea 3x, Hydrastis 3x.

PURPOSE SECTION

Formulated for symptoms associated with various types of incontinence such as stress incontinence, urge incontinence and overflow incontinence.

INACTIVE INGREDIENT SECTION

Inactive Ingredients: USP Purified Water; USP Gluten-free, non-GMO, organic cane dispensing alcohol 20%.

QUESTIONS? SECTION

www.newtonlabs.net Newton Laboratories, Inc. FDA Est # 1051203 - Conyers, GA 30012
Questions? 1.800.448.7256

WARNINGS SECTION

Warning: Do not use if tamper - evident seal is broken or missing. Consult a licensed healthcare professional if pregnant, nursing or if symptoms worsen or persist for more than a few days. Keep out of reach of children.

PREGNANCY OR BREAST FEEDING SECTION

Consult a licensed healthcare professional if pregnant or nursing or if symptoms worsen or persist for more than a few days.

KEEP OUT OF REACH OF CHILDREN SECTION

Keep out of reach of children.